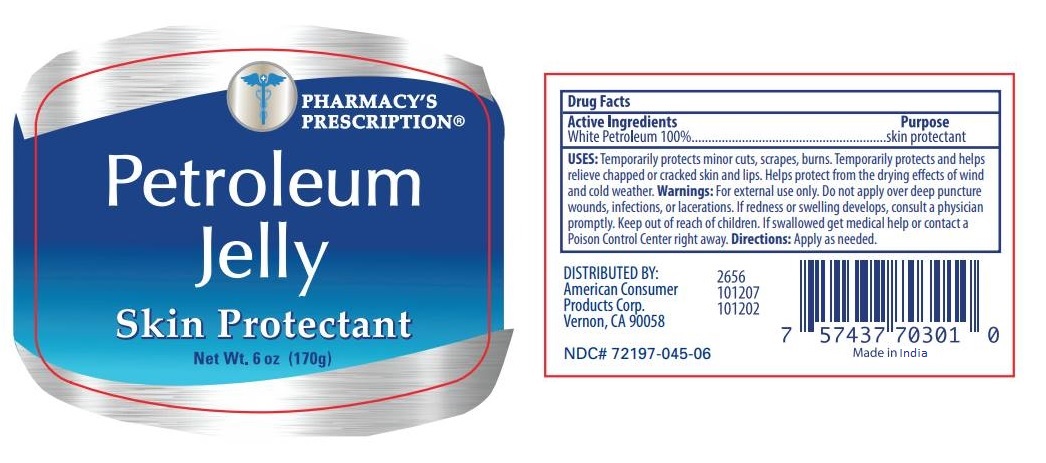 DRUG LABEL: Pharmacys Prescription Petroleum Jelly
NDC: 72197-045 | Form: GEL
Manufacturer: American Consumer Products Corp
Category: otc | Type: HUMAN OTC DRUG LABEL
Date: 20250709

ACTIVE INGREDIENTS: PETROLATUM 99.9 g/100 g
INACTIVE INGREDIENTS: WATER

Pharmacys Prescription Petroleum Jelly

Active Ingredients

White Petrolatum USP 100%

Inactive Ingredient

Inactive Ingredient • Fragrance

Purpose

Skin Protectant

Use

USES: Temporarily protects minor: cuts, scrapes, burns • Temporarily protects and helps relieve chapped or cracked skin and lips • Helps protect from the drying effects of wind and cold weather.

Warnings

Warnings: For external use only • Do not apply over deep puncture wounds, infections, or lacerations.

ASK DOCTOR

If redness or swelling develops, consult a physician promptly.

Keep out of reach of children • If swallowed get medical help or contact a Poison Control Center right away.

Directions

Directions: Apply as needed.

Other Information

DISTRIBUTED BY:

American Consumer

Products Corp.

Vernon, CA 90058

Made in India